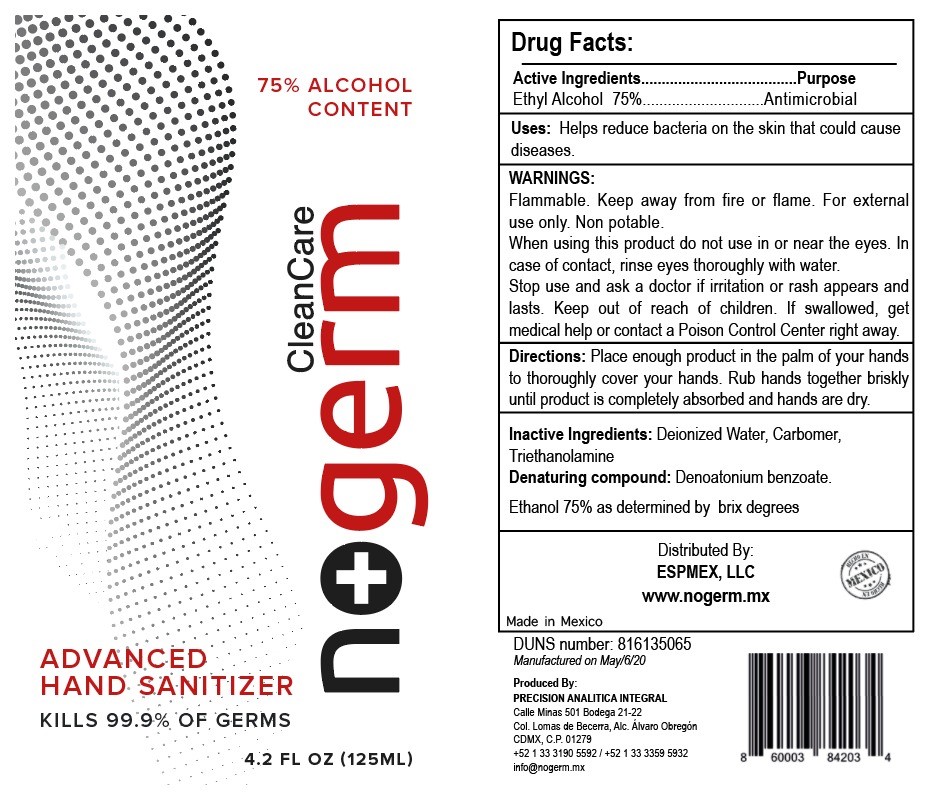 DRUG LABEL: HAND SANITIZER
NDC: 77492-006 | Form: GEL
Manufacturer: PRECISION ANALITICA INTEGRAL SA DE CV
Category: otc | Type: HUMAN OTC DRUG LABEL
Date: 20200602

ACTIVE INGREDIENTS: ALCOHOL 75 mL/100 mL
INACTIVE INGREDIENTS: CARBOMER HOMOPOLYMER, UNSPECIFIED TYPE; TROLAMINE; WATER

Active Ingredient(s)

Alcohol 75% vv

purpose

antiseptic: hand sanitizer

use

hand sanitizer to help reduce bacteria that potentially can cause disease. for use when soap and water are not available

warnings

for external use only. flammable. keep away from heat or flame

do not use

* in children less than 2 months of age

* on open skin wounds

* do not use in or near eyes

when using

when using this product keep out of eyes, ears, and mouth. In case of contact with eyes, rinse eyes thoroughly with water.

stop use and ask a doctor if irritation or rash occurs. These may be signs of a serious condition.

keep out of reach of children. if swallowed, get medical help or contact a Poison control center right away.

keep out of reach of children. if swallowed, get medical help or contact a poison control center right away.

directions

* Place enough product on hands to cover all surfaces. rub hands together until dry.

*Supervise children under 6 years of age when using this product to avoid swallowing.

other information

* store between 15-30c (59-86F)

* Avoid freezing and excessive heat above 40C (104F)

inactive ingredients

Carbormer, Trietanolamin, water

nogerm label-package label

ndc 77492-006-25

nogerm label 125 ml

hand sanitizer

kills 99.99% of all germs